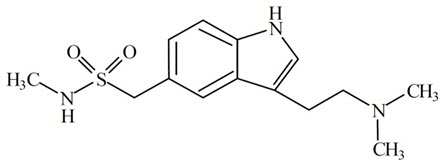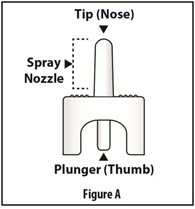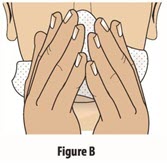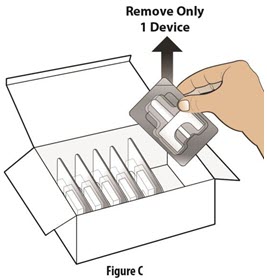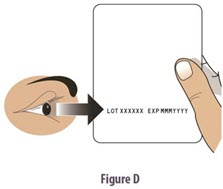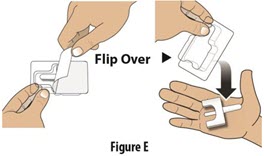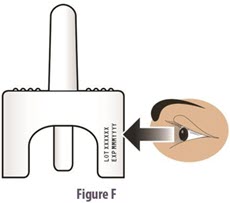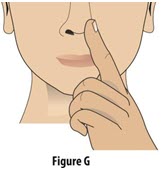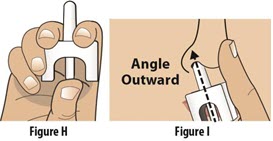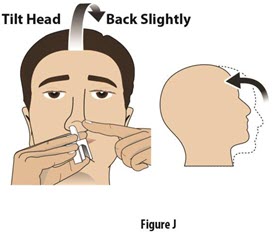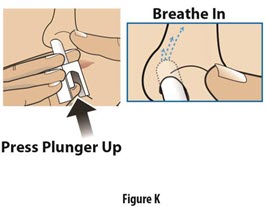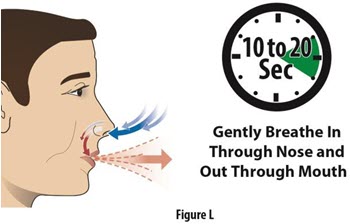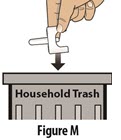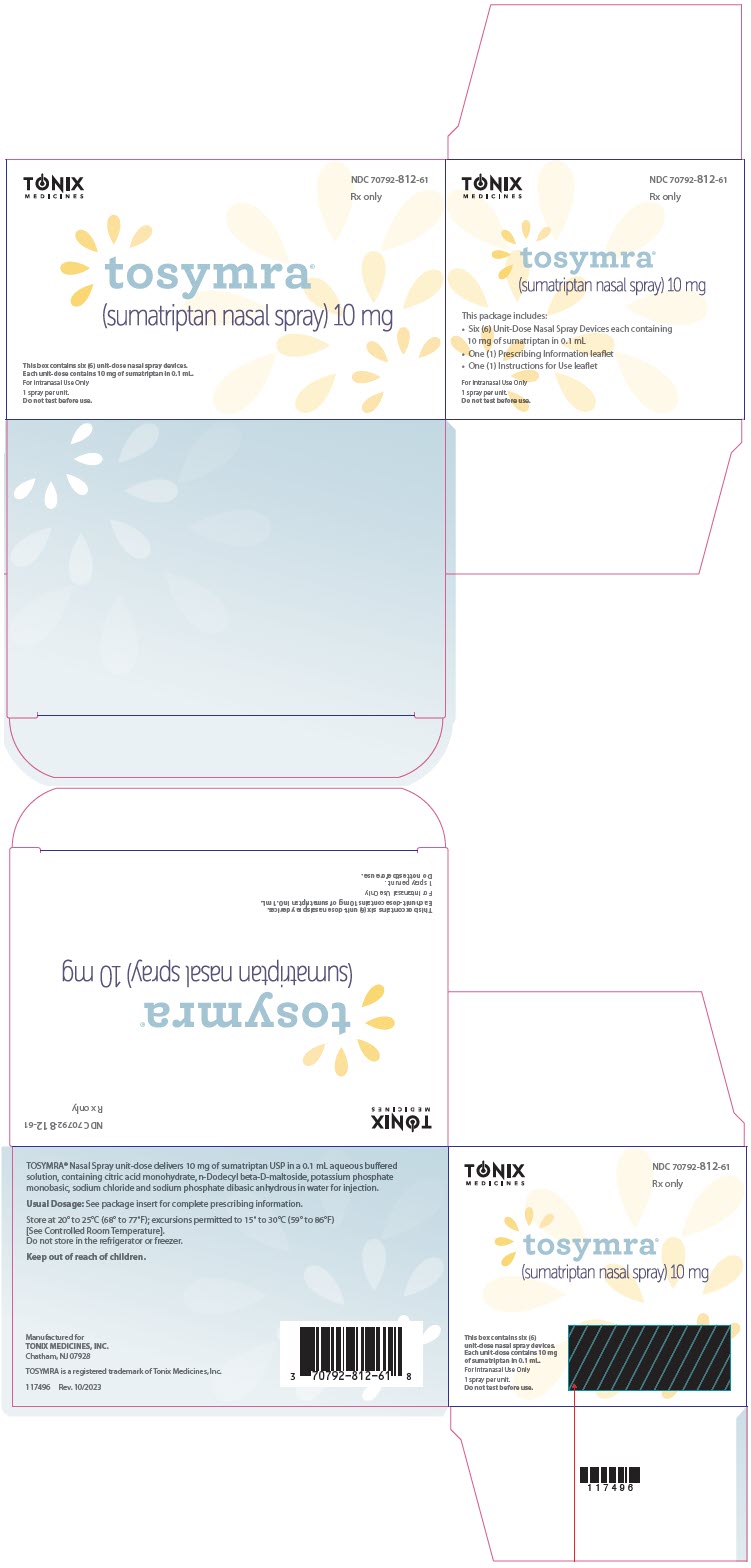 DRUG LABEL: Tosymra
NDC: 70792-812 | Form: SPRAY
Manufacturer: Tonix Medicines, Inc.
Category: prescription | Type: HUMAN PRESCRIPTION DRUG LABEL
Date: 20250221

ACTIVE INGREDIENTS: Sumatriptan 10 mg/0.1 mL
INACTIVE INGREDIENTS: CITRIC ACID MONOHYDRATE; N-DODECYL .BETA.-D-MALTOSIDE; MONOBASIC POTASSIUM PHOSPHATE; SODIUM CHLORIDE; SODIUM PHOSPHATE, DIBASIC, ANHYDROUS; WATER

HIGHLIGHTS OF PRESCRIBING INFORMATION

These highlights do not include all the information needed to use TOSYMRA® safely and effectively. See full prescribing information for TOSYMRA®.
TOSYMRA® (sumatriptan) nasal spray
Initial U.S. Approval: 1992

1 INDICATIONS AND USAGE

TOSYMRA is a serotonin (5-HT1B/1D) receptor agonist (triptan) indicated for the acute treatment of migraine with or without aura in adults (1)

Limitations of Use:

- Use only if a clear diagnosis of migraine has been established (1)
- Not indicated for the preventive treatment of migraine (1)
- Not indicated for the treatment of cluster headache (1)

2 DOSAGE AND ADMINISTRATION

- Single dose of 10 mg of nasal spray (2)
- Maximum dose in a 24-hour period: 30 mg; separate doses by at least one hour (2)

3 DOSAGE FORMS AND STRENGTHS

Nasal Spray, 10 mg (3)

4 CONTRAINDICATIONS

- History of coronary artery disease or coronary vasospasm (4)
- Wolff-Parkinson-White syndrome or other cardiac accessory conduction pathway disorders (4)
- History of stroke, transient ischemic attack, or hemiplegic or basilar migraine (4)
- Peripheral vascular disease (4)
- Ischemic bowel disease (4)
- Uncontrolled hypertension (4)
- Recent (within 24 hours) use of another 5-HT1 agonist (e.g., another triptan) or of an ergotamine-containing medication (4)
- Concurrent or recent (past 2 weeks) use of monoamine oxidase-A inhibitor (4)
- Hypersensitivity to sumatriptan (angioedema and anaphylaxis seen) (4)
- Severe hepatic impairment (4)

5 WARNINGS AND PRECAUTIONS

- Myocardial ischemia/infarction and Prinzmetal's angina: Perform cardiac evaluation in patients with multiple cardiovascular risk factors (5.1)
- Arrhythmias: Discontinue TOSYMRA if occurs (5.2)
- Chest/throat/neck/jaw pain, tightness, pressure, or heaviness: Generally, not associated with myocardial ischemia; evaluate for coronary artery disease in patients at high risk (5.3)
- Cerebral hemorrhage, subarachnoid hemorrhage, and stroke: Discontinue TOSYMRA if occurs (5.4)
- Gastrointestinal ischemia and reactions, peripheral vasospastic reactions: Discontinue TOSYMRA if occurs (5.5)
- Medication overuse headache: Detoxification may be necessary (5.6)
- Serotonin syndrome: Discontinue TOSYMRA if occurs (5.7)
- Increase in blood pressure: Hypertensive crisis can occur (5.8)
- Hypersensitivity reactions: Angioedema and anaphylaxis can occur (5.9)
- Seizures: Use with caution in patients with epilepsy or a lowered seizure threshold (5.10)
- Local irritation: Burning and abnormal taste can occur (5.11)

6 ADVERSE REACTIONS

Most common adverse reactions (≥5% and > placebo) with sumatriptan injection were tingling, dizziness/vertigo, warm/hot sensation, burning sensation, feeling of heaviness, pressure sensation, flushing, feeling of tightness, and numbness (6.1)

Additional common adverse reactions with TOSYMRA include application site reactions, dysgeusia, and throat irritation. (6.1)

To report SUSPECTED ADVERSE REACTIONS, contact Tonix Medicines, Inc. at 1-888-869-7633 (1-888-TNXPMED) or FDA at 1-800-FDA-1088 or www.fda.gov/medwatch.

8 USE IN SPECIFIC POPULATIONS

Pregnancy: Based on animal data, may cause fetal harm (8.1)

FULL PRESCRIBING INFORMATION

1 INDICATIONS AND USAGE

TOSYMRA is indicated for the acute treatment of migraine with or without aura in adults.

Limitations of Use:

- Use only if a clear diagnosis of migraine has been established. If a patient has no response to the first migraine attack treated with TOSYMRA, reconsider the diagnosis before TOSYMRA is administered to treat any subsequent attacks.
- TOSYMRA is not indicated for the preventive treatment of migraine.
- TOSYMRA is not indicated for the treatment of cluster headache.

2 DOSAGE AND ADMINISTRATION

The recommended dose of TOSYMRA is 10 mg given as a single spray in one nostril.

The maximum cumulative dose that may be given in a 24-hour period is 30 mg, with doses of TOSYMRA separated by at least 1 hour. TOSYMRA may also be given at least 1 hour following a dose of another sumatriptan product.

3 DOSAGE FORMS AND STRENGTHS

Single-dose nasal spray device delivering 10 mg of sumatriptan.

4 CONTRAINDICATIONS

TOSYMRA is contraindicated in patients with:

- Ischemic coronary artery disease (CAD) (angina pectoris, history of myocardial infarction, or documented silent ischemia) or coronary artery vasospasm, including Prinzmetal's angina [see Warnings and Precautions (5.1)].
- Wolff-Parkinson-White syndrome or arrhythmias associated with other cardiac accessory conduction pathway disorders [see Warnings and Precautions (5.2)].
- History of stroke or transient ischemic attack (TIA) or history of hemiplegic or basilar migraine because these patients are at a higher risk of stroke [see Warnings and Precautions (5.4)].
- Peripheral vascular disease [see Warnings and Precautions (5.5)].
- Ischemic bowel disease [see Warnings and Precautions (5.5)].
- Uncontrolled hypertension [see Warnings and Precautions (5.8)].
- Recent use (i.e., within 24 hours) of ergotamine-containing medication, ergot-type medication (such as dihydroergotamine or methysergide), or another 5-hydroxytryptamine1 (5-HT1) agonist [see Drug Interactions (7.1, 7.3)].
- Concurrent administration of a monoamine oxidase (MAO)-A inhibitor or recent (within 2 weeks) use of an MAO-A inhibitor [see Drug Interactions (7.2) and Clinical Pharmacology (12.3)].
- Hypersensitivity to sumatriptan (angioedema and anaphylaxis seen) [see Warnings and Precautions (5.9)].
- Severe hepatic impairment [see Clinical Pharmacology (12.3)].

5 WARNINGS AND PRECAUTIONS

5.1 Myocardial Ischemia, Myocardial Infarction, and Prinzmetal's Angina

The use of TOSYMRA is contraindicated in patients with ischemic or vasospastic CAD. There have been rare reports of serious cardiac adverse reactions, including acute myocardial infarction, occurring within a few hours following administration of sumatriptan. Some of these reactions occurred in patients without known CAD. 5-HT1 agonists, including TOSYMRA, may cause coronary artery vasospasm (Prinzmetal's angina), even in patients without a history of CAD.

Perform a cardiovascular evaluation in triptan-naive patients who have multiple cardiovascular risk factors (e.g., increased age, diabetes, hypertension, smoking, obesity, strong family history of CAD) prior to receiving TOSYMRA. If there is evidence of CAD or coronary artery vasospasm, TOSYMRA is contraindicated. For patients with multiple cardiovascular risk factors who have a negative cardiovascular evaluation, consider administering the first dose of TOSYMRA in a medically supervised setting and performing an electrocardiogram (ECG) immediately following administration of TOSYMRA. For such patients, consider periodic cardiovascular evaluation in intermittent long-term users of TOSYMRA.

5.2 Arrhythmias

Life-threatening disturbances of cardiac rhythm, including ventricular tachycardia and ventricular fibrillation leading to death, have been reported within a few hours following the administration of 5-HT1 agonists. Discontinue TOSYMRA if these disturbances occur.

TOSYMRA is contraindicated in patients with Wolff-Parkinson-White syndrome or arrhythmias associated with other cardiac accessory conduction pathway disorders.

5.3 Chest, Throat, Neck, and/or Jaw Pain/Tightness/Pressure

Sensations of tightness, pain, pressure, and heaviness in the precordium, throat, neck, and jaw commonly occur after treatment with sumatriptan injection and are usually non-cardiac in origin. However, perform a cardiac evaluation if these patients are at high cardiac risk. The use of TOSYMRA is contraindicated in patients shown to have CAD and those with Prinzmetal's variant angina.

5.4 Cerebrovascular Events

Cerebral hemorrhage, subarachnoid hemorrhage, and stroke have occurred in patients treated with 5-HT1 agonists, and some have resulted in fatalities. In a number of cases, it appears possible that the cerebrovascular events were primary, the 5-HT1 agonist having been administered in the incorrect belief that the symptoms experienced were a consequence of migraine when they were not. Also, patients with migraine may be at increased risk of certain cerebrovascular events (e.g., stroke, hemorrhage, TIA). Discontinue TOSYMRA if a cerebrovascular event occurs.

Before treating headaches in patients not previously diagnosed with migraine or in patients who present with atypical symptoms, exclude other potentially serious neurological conditions. TOSYMRA is contraindicated in patients with a history of stroke or TIA.

5.5 Other Vasospasm Reactions

TOSYMRA may cause non-coronary vasospastic reactions, such as peripheral vascular ischemia, gastrointestinal vascular ischemia and infarction (presenting with abdominal pain and bloody diarrhea), splenic infarction, and Raynaud's syndrome. In patients who experience symptoms or signs suggestive of non-coronary vasospasm reaction following the use of any 5-HT1 agonist, rule out a vasospastic reaction before receiving additional TOSYMRA.

Reports of transient and permanent blindness and significant partial vision loss have been reported with the use of 5-HT1 agonists. Since visual disorders may be part of a migraine attack, a causal relationship between these events and the use of 5-HT1 agonists have not been clearly established.

5.6 Medication Overuse Headache

Overuse of acute migraine drugs (e.g., ergotamine, triptans, opioids, or combination of these drugs for 10 or more days per month) may lead to exacerbation of headache (medication overuse headache). Medication overuse headache may present as migraine-like daily headaches, or as a marked increase in frequency of migraine attacks. Detoxification of patients, including withdrawal of the overused drugs, and treatment of withdrawal symptoms (which often includes a transient worsening of headache) may be necessary.

5.7 Serotonin Syndrome

Serotonin syndrome may occur with TOSYMRA, particularly during co-administration with selective serotonin reuptake inhibitors (SSRIs), serotonin norepinephrine reuptake inhibitors (SNRIs), tricyclic antidepressants (TCAs), and MAO inhibitors [see Drug Interactions (7.4)]. Serotonin syndrome symptoms may include mental status changes (e.g., agitation, hallucinations, coma), autonomic instability (e.g., tachycardia, labile blood pressure, hyperthermia), neuromuscular aberrations (e.g., hyperreflexia, incoordination), and/or gastrointestinal symptoms (e.g., nausea, vomiting, diarrhea). The onset of symptoms usually occurs within minutes to hours of receiving a new or a greater dose of a serotonergic medication. Discontinue TOSYMRA if serotonin syndrome is suspected.

5.8 Increase in Blood Pressure

Significant elevation in blood pressure, including hypertensive crisis with acute impairment of organ systems, has been reported on rare occasions in patients treated with 5-HT1 agonists, including patients without a history of hypertension. Monitor blood pressure in patients treated with TOSYMRA. TOSYMRA is contraindicated in patients with uncontrolled hypertension.

5.9 Hypersensitivity Reactions

Hypersensitivity reactions, including angioedema and anaphylaxis, have occurred in patients receiving sumatriptan. Such reactions can be life threatening or fatal. In general, anaphylactic reactions to drugs are more likely to occur in individuals with a history of sensitivity to multiple allergens. TOSYMRA is contraindicated in patients with a history of hypersensitivity reaction to sumatriptan.

5.10 Seizures

Seizures have been reported following administration of sumatriptan. Some have occurred in patients with either a history of seizures or concurrent conditions predisposing to seizures. There are also reports in patients where no such predisposing factors are apparent. TOSYMRA should be used with caution in patients with a history of epilepsy or conditions associated with a lowered seizure threshold.

5.11 Local Irritation

Local irritative symptoms were reported in approximately 46% of patients treated with TOSYMRA in an open-label trial which allowed repeated use of TOSYMRA over the course of 6 months. Of these, the most common local irritative symptoms were application site reaction (36%), dysgeusia (21%), and throat irritation (5%). Approximately 0.5% of the cases were reported as severe.

6 ADVERSE REACTIONS

The following serious adverse reactions are described below and elsewhere in the labeling:

- Myocardial Ischemia, Myocardial Infarction, and Prinzmetal's Angina [see Warnings and Precautions (5.1)]
- Arrhythmias [see Warnings and Precautions (5.2)]
- Chest, Throat, Neck, and/or Jaw Pain/Tightness/Pressure [see Warnings and Precautions (5.3)]
- Cerebrovascular Events [see Warnings and Precautions (5.4)]
- Other Vasospasm Reactions [see Warnings and Precautions (5.5)]
- Medication Overuse Headache [see Warnings and Precautions (5.6)]
- Serotonin Syndrome [see Warnings and Precautions (5.7)]
- Increase in Blood Pressure [see Warnings and Precautions (5.8)]
- Hypersensitivity Reactions [see Contraindications (4), Warnings and Precautions (5.9)]
- Seizures [see Warnings and Precautions (5.10)]
- Local Irritation [see Warnings and Precautions (5.11)]

6.1 Clinical Trials Experience

Because clinical trials are conducted under widely varying conditions, adverse reaction rates observed in the clinical trials of a drug cannot be directly compared with rates in the clinical trials of another drug and may not reflect the rates observed in practice.

Adverse Reactions in Placebo-Controlled Trials with Sumatriptan Injection

Table 1 lists adverse reactions that occurred in 2 placebo-controlled clinical trials in patients with migraine (Studies 2 and 3) following either a single 6 mg dose of sumatriptan injection or placebo. Only reactions that occurred at a frequency of 2% or more in groups treated with sumatriptan injection 6 mg and that occurred at a frequency greater than the placebo group are included in Table 1.

Table 1: Adverse Reactions in Pooled Placebo-Controlled Trials in Patients with Migraine (Studies 2 and 3)
Adverse Reaction | Sumatriptan Injection 6 mg Subcutaneous (n = 547) % | Placebo (n = 370) %
Atypical sensations | 42 | 9
Tingling | 14 | 3
Warm/hot sensation | 11 | 4
Burning sensation | 7 | <1
Feeling of heaviness | 7 | 1
Pressure sensation | 7 | 2
Feeling of tightness | 5 | <1
Numbness | 5 | 2
Feeling strange | 2 | <1
Tight feeling in head | 2 | <1
Cardiovascular
Flushing | 7 | 2
Chest discomfort | 5 | 1
Tightness in chest | 3 | <1
Pressure in chest | 2 | <1
Ear, nose, and throat
Throat discomfort | 3 | <1
Discomfort: nasal cavity/sinuses | 2 | <1
Miscellaneous
Jaw discomfort | 2 | 0
Musculoskeletal
Weakness | 5 | <1
Neck pain/stiffness | 5 | <1
Myalgia | 2 | <1
Neurological
Dizziness/vertigo | 12 | 4
Drowsiness/sedation | 3 | 2
Headache | 2 | <1
Skin
Sweating | 2 | 1

The incidence of adverse reactions in controlled clinical trials was not affected by gender or age of the patients. There were insufficient data to assess the impact of race on the incidence of adverse reactions.

Adverse Reactions in Studies with TOSYMRA

In an open-label study that was designed to evaluate the local tolerability of TOSYMRA, repeated use of TOSYMRA was allowed over the course of 6 months. In this study, local irritative symptoms were reported in approximately 46% of patients treated with TOSYMRA, the most common of which were application site reactions (e.g., burning sensations in the nose), dysgeusia, and throat irritation [see Warnings and Precautions (5.11)].

6.2 Post-marketing Experience

The following adverse reactions have been identified during post-approval use of sumatriptan tablets, sumatriptan nasal spray, and sumatriptan injection. Because these reactions are reported voluntarily from a population of uncertain size, it is not always possible to reliably estimate their frequency or establish a causal relationship to drug exposure.

Cardiovascular:

Hypotension, palpitations.

Neurological:

Dystonia, tremor.

7 DRUG INTERACTIONS

7.1 Ergot-Containing Drugs

Ergot-containing drugs have been reported to cause prolonged vasospastic reactions. Because these effects may be additive, use of ergotamine-containing or ergot-type medications (like dihydroergotamine or methysergide) and TOSYMRA within 24 hours of each other is contraindicated.

7.2 Monoamine Oxidase-A Inhibitors

MAO-A inhibitors increase systemic exposure by 2-fold. Therefore, the use of TOSYMRA in patients receiving MAO-A inhibitors is contraindicated [see Clinical Pharmacology (12.3)].

7.3 Other 5-HT1 Agonists

Because their vasospastic effects may be additive, coadministration of TOSYMRA and other 5-HT1 agonists (e.g., triptans) within 24 hours of each other is contraindicated.

7.4 Selective Serotonin Reuptake Inhibitors/Serotonin Norepinephrine Reuptake Inhibitors and Serotonin Syndrome

Cases of serotonin syndrome have been reported during co-administration of triptans and SSRIs, SNRIs, TCAs, and MAO inhibitors [see Warnings and Precautions (5.7)].

8 USE IN SPECIFIC POPULATIONS

8.1 Pregnancy

Risk Summary

Data from a prospective pregnancy exposure registry and epidemiological studies of pregnant women have not detected an increased frequency of birth defects or a consistent pattern of birth defects among women exposed to sumatriptan compared with the general population (see Data). In developmental toxicity studies in rats and rabbits, oral administration of sumatriptan to pregnant animals was associated with embryo lethality, fetal abnormalities, and pup mortality. When administered by the intravenous route to pregnant rabbits, sumatriptan was embryo lethal (see Data).

In the U.S. general population, the estimated background risk of major birth defects and of miscarriage in clinically recognized pregnancies is 2% to 4% and 15% to 20%, respectively. The reported rate of major birth defects among deliveries to women with migraine ranged from 2.2% to 2.9% and the reported rate of miscarriage was 17%, which were similar to rates reported in women without migraine.

Clinical Considerations

Disease-Associated Maternal and/or Embryo/Fetal Risk: Several studies have suggested that women with migraine may be at increased risk of preeclampsia during pregnancy.

Data

Human Data

The Sumatriptan/Naratriptan/Treximet (sumatriptan and naproxen sodium) Pregnancy Registry, a population-based international prospective study, collected data for sumatriptan from January 1996 to September 2012. The Registry documented outcomes of 626 infants and fetuses exposed to sumatriptan during pregnancy (528 with earliest exposure during the first trimester, 78 during the second trimester, 16 during the third trimester, and 4 unknown). The occurrence of major birth defects (excluding fetal deaths and induced abortions without reported defects and all spontaneous pregnancy losses) during first-trimester exposure to sumatriptan was 4.2% (20/478 [95% CI: 2.6% to 6.5%]) and during any trimester of exposure was 4.2% (24/576 [95% CI: 2.7% to 6.2%]). The sample size in this study had 80% power to detect at least a 1.73- to 1.91-fold increase in the rate of major malformations. The number of exposed pregnancy outcomes accumulated during the registry was insufficient to support definitive conclusions about overall malformation risk or for making comparisons of the frequencies of specific birth defects. Of the 20 infants with reported birth defects after exposure to sumatriptan in the first trimester, 4 infants had ventricular septal defects, including one infant who was exposed to both sumatriptan and naratriptan, and 3 infants had pyloric stenosis. No other birth defect was reported for more than 2 infants in this group.

In a study using data from the Swedish Medical Birth Register, live births to women who reported using triptans or ergots during pregnancy were compared with those of women who did not. Of the 2,257 births with first-trimester exposure to sumatriptan, 107 infants were born with malformations (relative risk 0.99 [95% CI: 0.91 to 1.21]). A study using linked data from the Medical Birth Registry of Norway to the Norwegian Prescription Database compared pregnancy outcomes in women who redeemed prescriptions for triptans during pregnancy, as well as a migraine disease comparison group who redeemed prescriptions for sumatriptan before pregnancy only, compared with a population control group. Of the 415 women who redeemed prescriptions for sumatriptan during the first trimester, 15 had infants with major congenital malformations (OR 1.16 [95% CI: 0.69 to 1.94]) while for the 364 women who redeemed prescriptions for sumatriptan before, but not during, pregnancy, 20 had infants with major congenital malformations (OR 1.83 [95% CI: 1.17 to 2.88]), each compared with the population comparison group. Additional smaller observational studies evaluating use of sumatriptan during pregnancy have not suggested an increased risk of teratogenicity.

Animal Data

Oral administration of sumatriptan to pregnant rats during the period of organogenesis resulted in an increased incidence of fetal blood vessel (cervicothoracic and umbilical) abnormalities. The highest no-effect dose for embryofetal developmental toxicity in rats was 60 mg/kg/day. Oral administration of sumatriptan to pregnant rabbits during the period of organogenesis resulted in increased incidences of embryo lethality and fetal cervicothoracic vascular and skeletal abnormalities. Intravenous administration of sumatriptan to pregnant rabbits during the period of organogenesis resulted in an increased incidence of embryo lethality. The highest oral and intravenous no-effect doses for developmental toxicity in rabbits were 15 and 0.75 mg/kg/day, respectively.

Oral administration of sumatriptan to rats prior to and throughout gestation resulted in embryofetal toxicity (decreased body weight, decreased ossification, increased incidence of skeletal abnormalities). The highest no-effect dose was 50 mg/kg/day. In offspring of pregnant rats treated orally with sumatriptan during organogenesis, there was a decrease in pup survival. The highest no-effect dose for this effect was 60 mg/kg/day. Oral treatment of pregnant rats with sumatriptan during the latter part of gestation and throughout lactation resulted in a decrease in pup survival. The highest no-effect dose for this finding was 100 mg/kg/day.

8.2 Lactation

Risk Summary

Sumatriptan is excreted in human milk following subcutaneous administration (see Data). There are no data on the effects of sumatriptan on the breastfed infant or the effects of sumatriptan on milk production.

The developmental and health benefits of breastfeeding should be considered along with the mother's clinical need for TOSYMRA and any potential adverse effects on the breastfed infant from sumatriptan or from the underlying maternal condition.

Clinical Considerations

Infant exposure to sumatriptan can be minimized by avoiding breastfeeding for 12 hours after treatment with TOSYMRA.

Data

Following subcutaneous administration of a 6 mg dose of sumatriptan injection in 5 lactating volunteers, sumatriptan was present in milk.

8.4 Pediatric Use

Safety and effectiveness of TOSYMRA in pediatric patients have not been established. TOSYMRA is not recommended for use in patients younger than 18 years of age.

Two controlled clinical trials evaluated sumatriptan nasal spray (5 mg to 20 mg) in 1,248 pediatric migraineurs 12 to 17 years of age who treated a single attack. The trials did not establish the efficacy of sumatriptan nasal spray compared with placebo in the treatment of migraine in pediatric patients. Adverse reactions observed in these clinical trials were similar in nature to those reported in clinical trials in adults.

Five controlled clinical trials (2 single-attack trials, 3 multiple-attack trials) evaluating oral sumatriptan (25 mg to 100 mg) in pediatric subjects 12 to 17 years of age enrolled a total of 701 pediatric migraineurs. These trials did not establish the efficacy of oral sumatriptan compared with placebo in the treatment of migraine in pediatric patients. Adverse reactions observed in these clinical trials were similar in nature to those reported in clinical trials in adults. The frequency of all adverse reactions in these patients appeared to be both dose- and age-dependent, with younger patients reporting reactions more commonly than older pediatric patients.

Post-marketing experience documents that serious adverse reactions have occurred in the pediatric population after use of subcutaneous, oral, and/or intranasal sumatriptan. These reports include reactions similar in nature to those reported rarely in adults, including stroke, visual loss, and death. A myocardial infarction has been reported in a 14-year-old male following the use of oral sumatriptan; clinical signs occurred within 1 day of drug administration. Clinical data to determine the frequency of serious adverse reactions in pediatric patients who might receive subcutaneous, oral, or intranasal sumatriptan are not presently available.

8.5 Geriatric Use

Clinical trials of sumatriptan did not include sufficient numbers of subjects aged 65 and over to determine whether they respond differently from younger patients. Other reported clinical experience has not identified differences in responses between the elderly and younger subjects. In general, dose selection for an elderly patient should be cautious, usually starting at the low end of the dosing range, reflecting the greater frequency of decreased hepatic, renal, or cardiac function and of concomitant disease or other drug therapy.

A cardiovascular evaluation is recommended for geriatric patients who have other cardiovascular risk factors (e.g., diabetes, hypertension, smoking, obesity, strong family history of CAD) prior to receiving TOSYMRA [see Warnings and Precautions (5.1)].

10 OVERDOSAGE

Coronary vasospasm was observed after intravenous administration of sumatriptan injection [see Contraindications (4)]. Overdoses would be expected from animal data (dogs at 0.1 g/kg, rats at 2 g/kg) to possibly cause convulsions, tremor, inactivity, erythema of the extremities, reduced respiratory rate, cyanosis, ataxia, mydriasis, injection site reactions (desquamation, hair loss, and scab formation), and paralysis.

The elimination half-life of sumatriptan is about 2 hours [see Clinical Pharmacology (12.3)], and therefore monitoring of patients after overdose with TOSYMRA should continue for at least 10 hours or while symptoms or signs persist.

It is unknown what effect hemodialysis or peritoneal dialysis has on the serum concentrations of sumatriptan.

11 DESCRIPTION

TOSYMRA contains sumatriptan, a selective 5-HT1B/1D receptor agonist. Sumatriptan is chemically designated as 1-[3-[2-(dimethylamino)ethyl]-1H-indol-5-yl]-N-methylmethanesulfonamide, and it has the following structure:

The empirical formula is C14H21N3O2S, representing a molecular weight of 295.40. Sumatriptan is a white to pale yellow powder that is very slightly soluble in water.

TOSYMRA nasal spray is a clear, pale yellow to yellow colored liquid. Each 100 uL of TOSYMRA contains 10 mg of sumatriptan in single-dose aqueous buffered solution containing citric acid monohydrate, n-Dodecyl beta-D-maltoside, potassium phosphate monobasic, sodium chloride, and sodium phosphate dibasic anhydrous in water for injection.

The pH range of solution is approximately 5.0 to 6.0 and the osmolality is between 270 to 330 mOsmol.

12 CLINICAL PHARMACOLOGY

12.1 Mechanism of Action

Sumatriptan binds with high affinity to human cloned 5-HT1B/1D receptors. Sumatriptan presumably exerts its therapeutic effects in the treatment of migraine headache through agonist effects at the 5-HT1B/1D receptors on intracranial blood vessels and sensory nerves of the trigeminal system, which result in cranial vessel constriction and inhibition of pro-inflammatory neuropeptide release.

12.2 Pharmacodynamics

Blood Pressure

Significant elevation in blood pressure, including hypertensive crisis, has been reported in patients with and without a history of hypertension [see Warnings and Precautions (5.8)].

Peripheral (Small) Arteries

In healthy volunteers (N = 18), a trial evaluating the effects of sumatriptan on peripheral (small vessel) arterial reactivity failed to detect a clinically significant increase in peripheral resistance.

Heart Rate

Transient increases in blood pressure observed in some subjects in clinical trials carried out during sumatriptan's development as a treatment for migraine were not accompanied by any clinically significant changes in heart rate.

12.3 Pharmacokinetics

Following nasal administration of 10 mg TOSYMRA in 73 healthy subjects, the relative bioavailability of TOSYMRA was approximately 87% [90% confidence interval (CI) 82 to 94] of that obtained following 4 mg subcutaneous injection of sumatriptan. The relative bioavailability of TOSYMRA was 58% [90% CI 55 to 62] following 6 mg subcutaneous injection of sumatriptan.

Absorption

Peak plasma concentration of sumatriptan was observed in a median time of 10 minutes (range 5 to 23 minutes). After single nasal administration of the 10 mg dose, the mean (CV%) Cmax and AUC were 51.8 ng/mL (58%) and 60.70 ng•hr/mL (42%), respectively.

Distribution

Sumatriptan protein binding, determined by equilibrium dialysis over the concentration range of 10 to 1,000 ng/mL, is low, approximately 14% to 21%. The effect of sumatriptan on the protein binding of other drugs has not been evaluated.

Following a 6-mg subcutaneous injection into the deltoid area of the arm in 9 males (mean age: 33 years, mean weight: 77 kg) the volume of distribution central compartment of sumatriptan was 50 ± 8 liters and the distribution half-life was 15 ± 2 minutes.

Elimination

The elimination half-life of sumatriptan following administration of TOSYMRA is 2.44 ± 1.00 hours.

Metabolism

In vitro studies with human microsomes suggest that sumatriptan is metabolized by MAO, predominantly the A isoenzyme. Most of a radiolabeled dose of sumatriptan excreted in the urine is the major metabolite indole acetic acid (IAA) or the IAA glucuronide, both of which are inactive.

Excretion

After a single 6 mg subcutaneous dose, 22% ± 4% was excreted in the urine as unchanged sumatriptan and 38% ± 7% as the IAA metabolite.

Following a 6 mg subcutaneous injection into the deltoid area of the arm, the systemic clearance of sumatriptan was 1,194 ± 149 mL/min and the terminal half-life was 115 ± 19 minutes.

Specific Populations

Age

The pharmacokinetics of sumatriptan in the elderly (mean age: 72 years, 2 males and 4 females) and in subjects with migraine (mean age: 38 years, 25 males and 155 females) were similar to that in healthy male subjects (mean age: 30 years).

Patients with Hepatic Impairment

The effect of hepatic disease on the pharmacokinetics of TOSYMRA has not been evaluated. The effect of mild to moderate hepatic disease on the pharmacokinetics of subcutaneously administered sumatriptan has been evaluated. There were no significant differences in the pharmacokinetics of subcutaneously administered sumatriptan in moderately hepatically impaired subjects compared with healthy controls. The pharmacokinetics of subcutaneously administered sumatriptan in patients with severe hepatic impairment has not been studied. The use of TOSYMRA in this population is contraindicated [see Contraindications (4)].

Racial Groups

The systemic clearance and Cmax of subcutaneous sumatriptan were similar in black (n=34) and Caucasian (n=38) healthy male subjects. TOSYMRA has not been evaluated for race differences.

Drug Interaction Studies

Monoamine Oxidase-A Inhibitors

In a trial of 14 healthy females, pretreatment with an MAO-A inhibitor decreased the clearance of subcutaneous sumatriptan, resulting in a 2-fold increase in the area under the sumatriptan plasma concentration-time curve (AUC), corresponding to a 40% increase in elimination half-life.

13 NONCLINICAL TOXICOLOGY

13.1 Carcinogenesis, Mutagenesis, Impairment of Fertility

Carcinogenesis

In carcinogenicity studies in mouse and rat, sumatriptan was administered orally for 78 weeks and 104 weeks, respectively, at doses up to 160 mg/kg/day (the highest dose in rat was reduced from 360 mg/kg/day during Week 21). There was no evidence in either species of an increase in tumors related to sumatriptan administration.

Mutagenesis

Sumatriptan was negative in in vitro (bacterial reverse mutation [Ames], gene cell mutation in Chinese hamster V79/HGPRT, chromosomal aberration in human lymphocytes) and in vivo (rat micronucleus) assays.

Impairment of Fertility

When sumatriptan (0, 5, 50, 500 mg/kg/day) was administered orally to male and female rats prior to and throughout the mating period, there was a treatment-related decrease in fertility secondary to a decrease in mating in animals treated with doses greater than 5 mg/kg/day. It is not clear whether this finding was due to an effect on males or females or both.

When sumatriptan was administered by subcutaneous injection to male and female rats prior to and throughout the mating period, there was no evidence of impaired fertility at doses up to 60 mg/kg/day.

13.2 Animal Toxicology and/or Pharmacology

Corneal Opacities

Dogs receiving oral sumatriptan developed corneal opacities and defects in the corneal epithelium. Corneal opacities were seen at the lowest dose tested, 2 mg/kg/day, and were present after 1 month of treatment. Defects in the corneal epithelium were noted in a 60-week study. Earlier examinations for these toxicities were not conducted and no-effect doses were not established.

14 CLINICAL STUDIES

The efficacy of TOSYMRA is based on the relative bioavailability of TOSYMRA nasal spray compared to sumatriptan subcutaneous injection (4 mg) in healthy adults [see Clinical Pharmacology (12.3)].

In controlled clinical trials enrolling more than 1,000 patients during migraine attacks who were experiencing moderate or severe pain and 1 or more of the symptoms enumerated in Table 3, onset of relief began as early as 10 minutes following a 6 mg sumatriptan injection. Lower doses of sumatriptan injection may also prove effective, although the proportion of patients obtaining adequate relief was decreased and the latency to that relief is greater with lower doses.

In Study 1, 6 different doses of sumatriptan injection (n = 30 each group) were compared with placebo (n = 62) in a single-attack, parallel-group design; the dose-response relationship was found to be as shown in Table 2.

Table 2: Proportion of Patients with Migraine Relief and Incidence of Adverse Reactions by Time and by Sumatriptan Dose in Study 1
Dose of sumatriptan Injection | Percent Patients with Relief [Relief is defined as the reduction of moderate or severe pain to no or mild pain after dosing without use of rescue medication.] |  |  |  | Adverse Reactions Incidence (%)
Dose of sumatriptan Injection | at 10 Minutes | at 30 Minutes | at 1 Hour | at 2 Hours | Adverse Reactions Incidence (%)
Placebo | 5 | 15 | 24 | 21 | 55
1 mg | 10 | 40 | 43 | 40 | 63
2 mg | 7 | 23 | 57 | 43 | 63
3 mg | 17 | 47 | 57 | 60 | 77
4 mg [Efficacy of Tosymra nasal spray was demonstrated based on bioavailability to 4 mg sumatriptan SC injection.] | 13 | 37 | 50 | 57 | 80
6 mg | 10 | 63 | 73 | 70 | 83
8 mg | 23 | 57 | 80 | 83 | 93

In 2 randomized, placebo-controlled clinical trials of sumatriptan injection 6 mg in 1,104 patients with moderate or severe migraine pain (Studies 2 and 3), the onset of relief was less than 10 minutes. Headache relief, as defined by a reduction in pain from severe or moderately severe to mild or no headache, was achieved in 70% of the patients within 1 hour of a single 6 mg subcutaneous dose of sumatriptan injection. Approximately 82% and 65% of patients treated with sumatriptan 6 mg had headache relief and were pain free within 2 hours, respectively.

Table 3 shows the 1- and 2-hour efficacy results for sumatriptan injection 6 mg in Studies 2 and 3.

Table 3: Proportion of Patients with Pain Relief and Relief of Migraine Symptoms after 1 and 2 Hours of Treatment in Studies 2 and 3
1-Hour Data | Study 2 |  | Study 3
1-Hour Data | Placebo (n = 190) | Sumatriptan Injection 6 mg (n = 384) | Placebo (n = 180) | Sumatriptan Injection 6 mg (n = 350)
Patients with pain relief (Grade 0/1) | 18% | 70% [P<0.05 versus placebo.] | 26% | 70%
Patients with no pain | 5% | 48% | 13% | 49%
Patients without nausea | 48% | 73% | 50% | 73%
Patients without photophobia | 23% | 56% | 25% | 58%
Patients with little or no clinical disability [A successful outcome in terms of clinical disability was defined prospectively as ability to work mildly impaired or ability to work and function normally.] | 34% | 76% | 34% | 76%
2-Hour Data | Study 2 |  | Study 3
2-Hour Data | Placebo [Includes patients that may have received an additional placebo injection 1 hour after the initial injection.] | Sumatriptan Injection 6 mg [Includes patients that may have received an additional 6 mg of sumatriptan injection 1 hour after the initial injection.] | Placebo | Sumatriptan Injection 6 mg
Patients with pain relief (Grade 0/1) | 31% | 81% | 39% | 82%
Patients with no pain | 11% | 63% | 19% | 65%
Patients without nausea | 56% | 82% | 63% | 81%
Patients without photophobia | 31% | 72% | 35% | 71%
Patients with little or no clinical disability | 42% | 85% | 49% | 84%

Sumatriptan injection also relieved photophobia, phonophobia (sound sensitivity), nausea, and vomiting associated with migraine attacks.

The efficacy of sumatriptan injection was unaffected by whether or not the migraine was associated with aura, duration of attack, gender or age of the patient, or concomitant use of common migraine prophylactic drugs (e.g., beta-blockers).

16 HOW SUPPLIED/STORAGE AND HANDLING

16.1 How Supplied

- TOSYMRA® 10 mg (NDC 70792-812-89) contains sumatriptan and is supplied as a ready-to-use, single-dose, disposable unit.
- Each carton contains 6 units (NDC 70792-812-61) and a Patient Information and Instructions for Use leaflet.

16.2 Storage and Handling

Store at 20° to 25°C (68° to 77°F); excursions permitted between 15° to 30°C (59° to 86°F).

Do not store in the refrigerator or freezer. Do not test before use.

17 PATIENT COUNSELING INFORMATION

Advise the patient to read the FDA-approved patient labeling (Patient Information and Instructions for Use).

Risk of Myocardial Ischemia and/or Infarction, Prinzmetal's Angina, Other Vasospasm-Related Events, Arrhythmias, and Cerebrovascular Events

Inform patients that TOSYMRA may cause serious cardiovascular side effects such as myocardial infarction or stroke. Although serious cardiovascular events can occur without warning symptoms, patients should be alert for the signs and symptoms of chest pain, shortness of breath, irregular heartbeat, significant rise in blood pressure, weakness, and slurring of speech and should ask for medical advice when observing any indicative sign or symptoms are observed. Apprise patients of the importance of this follow-up [see Warnings and Precautions (5.1, 5.2, 5.4, 5.5, 5.8)].

Hypersensitivity Reactions

Inform patients that anaphylactic reactions have occurred in patients receiving sumatriptan. Such reactions can be life threatening or fatal. In general, anaphylactic reactions to drugs are more likely to occur in individuals with a history of sensitivity to multiple allergens [see Contraindications (4) and Warnings and Precautions (5.9)].

Concomitant Use with Other Triptans or Ergot Medications

Inform patients that use of TOSYMRA within 24 hours of another triptan or an ergot-type medication (including dihydroergotamine or methylsergide) is contraindicated [see Contraindications (4), Drug Interactions (7.1, 7.3)].

Serotonin Syndrome

Caution patients about the risk of serotonin syndrome with the use of TOSYMRA or other triptans, particularly during combined use with SSRIs, SNRIs, TCAs, and MAO inhibitors [see Warnings and Precautions (5.7), Drug Interactions (7.4)].

Medication Overuse Headache

Inform patients that use of acute migraine drugs for 10 or more days per month may lead to an exacerbation of headache and encourage patients to record headache frequency and drug use (e.g., by keeping a headache diary) [see Warnings and Precautions (5.6)].

Pregnancy

Advise patients to notify their healthcare provider if they become pregnant during treatment or plan to become pregnant [see Use in Specific Populations (8.1)].

Lactation

Advise patients to notify their healthcare provider if they are breastfeeding or plan to breastfeed [see Use in Specific Populations (8.2)].

Ability to Perform Complex Tasks

Treatment with TOSYMRA may cause somnolence and dizziness; instruct patients to evaluate their ability to perform complex tasks during migraine attacks and after administration of TOSYMRA.

Local Irritation

Inform patients that they may experience local irritation of their nose, mouth, and throat; and changes in taste [see Warnings and Precautions (5.11)].

How to Use TOSYMRA

Provide patients instruction on the proper use of TOSYMRA. Caution patients to avoid spraying the contents of the device in their eyes.

Manufactured for
TONIX MEDICINES, INC..Chatham, NJ 07928

TOSYMRA is a registered trademark of Tonix Medicines, Inc.

This product may be covered by one or more U.S. patent(s).

Revised: 10/2023

Patient Information
TOSYMRA® (toe-SIM-ruh)
(sumatriptan)
Nasal Spray

What is the most important information I should know about TOSYMRA?
TOSYMRA can cause serious side effects, including:
Heart attack and other heart problems. Heart problems may lead to death.
Stop taking TOSYMRA and get emergency medical help right away if you have any of the following symptoms of a heart attack:

- discomfort in the center of your chest that lasts for more than a few minutes, or that goes away and comes back
- severe tightness, pain, pressure, or heaviness in your chest, throat, neck, or jaw
- pain or discomfort in your arms, back, neck, jaw, or stomach
- shortness of breath with or without chest discomfort
- breaking out in a cold sweat
- nausea or vomiting
- feeling lightheaded

TOSYMRA is not for people with risk factors for heart disease unless a heart exam is done and shows no problem. You have a higher risk for heart disease if you:

- have high blood pressure
- have high cholesterol levels
- smoke
- are overweight
- have diabetes
- have a family history of heart disease

What is TOSYMRA?
TOSYMRA is a prescription medicine used to treat acute migraine headaches with or without aura in adults.
TOSYMRA is not used to treat other types of headaches such as hemiplegic (that make you unable to move on one side of your body) or basilar (rare form of migraine with aura) migraines.
TOSYMRA is not used to prevent or decrease the number of migraines you have. TOSYMRA is not used to treat cluster headaches.
It is not known if TOSYMRA is safe and effective in children under 18 years of age.

Do not take TOSYMRA if you have:

- heart problems or a history of heart problems
- narrowing of blood vessels to your legs, arms, stomach, or kidney (peripheral vascular disease)
- uncontrolled high blood pressure
- severe liver problems
- hemiplegic migraines or basilar migraines. If you are not sure if you have these types of migraines, ask your healthcare provider.
- had a stroke, transient ischemic attacks (TIAs), or problems with your blood circulation
- taken any of the following medicines in the last 24 hours:
  - almotriptan
  - eletriptan
  - frovatriptan
  - naratriptan
  - rizatriptan
  - ergotamines
  - dihydroergotamine
  Ask your healthcare provider if you are not sure if your medicine is listed above.

- are taking certain antidepressants, known as monoamine oxidase (MAO)-A inhibitors or it has been 2 weeks or less since you stopped taking a MAO-A inhibitor. Ask your healthcare provider or pharmacist for a list of these medicines if you are not sure.
- an allergy to sumatriptan or any of the ingredients in TOSYMRA. See the end of this Patient Information leaflet for a complete list of ingredients in TOSYMRA.

Before taking TOSYMRA, tell your healthcare provider about all of your medical conditions, including if you:

- have high blood pressure.
- have high cholesterol.
- have diabetes.
- smoke.
- are overweight.
- have heart problems or family history of heart problems or stroke.
- have kidney problems.
- have liver problems.
- have had epilepsy or seizures.
- are not using effective birth control.
- are pregnant or plan to become pregnant. It is not known if TOSYMRA can harm your unborn baby.
- are breastfeeding or plan to breastfeed. TOSYMRA passes into your breast milk. It is not known if this can harm your baby. Talk with your healthcare provider about the best way to feed your baby if you take TOSYMRA.

Tell your healthcare provider about all the medicines you take, including prescription and over-the-counter medicines, vitamins, and herbal supplements.
TOSYMRA and certain other medicines can affect each other, causing serious side effects.
Especially tell your healthcare provider if you take anti-depressant medicines called:

- selective serotonin reuptake inhibitors (SSRIs)
- serotonin norepinephrine reuptake inhibitors (SNRIs)
- tricyclic antidepressants (TCAs)
- monoamine oxidase inhibitors (MAOIs)

Ask your healthcare provider or pharmacist for a list of these medicines if you are not sure.
Know the medicines you take. Keep a list of them to show your healthcare provider or pharmacist when you get a new medicine.

How should I take TOSYMRA?

- See the Instructions for Use for complete information on how to use TOSYMRA nasal spray.
- Certain people should take their first dose of TOSYMRA in their healthcare provider's office or in another medical setting. Ask your healthcare provider if you should take your first dose in a medical setting.
- Use TOSYMRA exactly as your healthcare provider tells you to use it.
- You should take TOSYMRA as soon as the symptoms of your headache start, but it may be taken at any time during a migraine.
- If your headache comes back after the first nasal spray or you only get some relief from your headache, you can use a second nasal spray 1 hour after the first nasal spray.
- Do not use more than 30 mg of TOSYMRA Nasal Spray in a 24-hour period.
- If you use too much TOSYMRA, call your healthcare provider or go to the nearest hospital emergency room right away.
- You should write down when you have headaches and when you take TOSYMRA, so you can talk with your healthcare provider about how TOSYMRA is working for you.

What should I avoid while taking TOSYMRA?
TOSYMRA can cause dizziness, weakness, or drowsiness. If you have these symptoms, do not drive a car, use machinery, or do anything where you need to be alert.

What are the possible side effects of TOSYMRA?
TOSYMRA may cause serious side effects. See "What is the most important information I should know about TOSYMRA?"
These serious side effects include:

- changes in color or sensation in your fingers and toes (Raynaud's syndrome)
- stomach and intestinal problems (gastrointestinal and colonic ischemic events). Symptoms of gastrointestinal and colonic ischemic events include:
  - sudden or severe stomach pain
  - stomach pain after meals
  - weight loss
  - nausea or vomiting
  - constipation or diarrhea
  - bloody diarrhea
  - fever
- problems with blood circulation to your legs and feet (peripheral vascular ischemia). Symptoms of peripheral vascular ischemia include:
  - cramping and pain in your legs or hips
  - feeling of heaviness or tightness in your leg muscles
  - burning or aching pain in your feet or toes while resting
  - numbness, tingling, or weakness in your legs
  - cold feeling or color changes in 1 or both legs or feet
- medication overuse headaches. Some people who use too much migraine medicine, such as TOSYMRA, for 10 or more days each month may have worse headaches (medication overuse headache). If your headaches get worse, your healthcare provider may decide to stop your treatment with TOSYMRA.
- serotonin syndrome. Serotonin syndrome is a rare but serious problem that can happen in people using TOSYMRA, especially if TOSYMRA is used with anti-depressant medicines called SSRIs or SNRIs. Call your healthcare provider right away if you have any of the following symptoms of serotonin syndrome:
  - mental changes such as seeing things that are not there (hallucinations), agitation, or coma
  - fast heartbeat
  - changes in blood pressure
  - high body temperature
  - tight muscles
  - trouble walking
- increased blood pressure including a sudden severe increase (hypertensive crisis) even if you have no history of high blood pressure.
- hives (itchy bumps); swelling of your tongue, mouth, or throat.
- seizures. Seizures have happened in people taking TOSYMRA who have never had seizures before. Talk with your healthcare provider about your chance of having seizures while you take TOSYMRA.

The most common side effects of TOSYMRA include:

- tingling
- feeling of heaviness
- numbness

- dizziness
- feeling of pressure
- application site (nasal) reactions

- feeling warm or hot
- flushing
- abnormal taste

- burning feeling
- feeling of tightness
- throat irritation

Tell your healthcare provider if you have any side effect that bothers you or that does not go away.
These are not all the possible side effects of TOSYMRA. For more information, ask your healthcare provider or pharmacist.
Call your doctor for medical advice about side effects. You may report side effects to FDA at 1-800-FDA-1088.

How should I store TOSYMRA?

- Store between 68° to 77°F (20° to 25°C)
- Do not store in the refrigerator or freeze.
- Do not test before use.

Keep TOSYMRA and all medicines out of the reach of children.

General information about the safe and effective use of TOSYMRA.
Medicines are sometimes prescribed for purposes other than those listed in Patient Information leaflets. Do not use TOSYMRA for a condition for which it was not prescribed. Do not give TOSYMRA to other people, even if they have the same symptoms you have. It may harm them.
You can ask your healthcare provider or pharmacist for information about TOSYMRA that is written for healthcare professionals.
For more information, go to www.TOSYMRA.com or call 1-888-869-7633 (1-888-TNXPMED).

What are the ingredients in TOSYMRA?
Active ingredient: sumatriptan
Inactive ingredients: citric acid monohydrate, n-Dodecyl beta-D-maltoside, potassium phosphate monobasic, sodium chloride, and sodium phosphate dibasic anhydrous in water for injection.
Manufactured for
TONIX MEDICINES, INC.
Chatham, NJ 07928
TOSYMRA is a registered trademark of Tonix Medicines, Inc.
This product may be covered by one or more U.S. patent(s).

This Patient Information has been approved by the U.S. Food and Drug Administration.

Revised: 10/2023

Instructions for Use
TOSYMRA® (toe-SIM-ruh)
(sumatriptan)
Nasal Spray

About TOSYMRA

Important Information

Read this Instructions for Use before you start using TOSYMRA and each time you get a refill. There may be new information. This information does not take the place of talking to your healthcare provider about your medical condition or treatment. If you have any questions about TOSYMRA, ask your healthcare provider or pharmacist.

- Only 1 device is needed to deliver a full dose (See Figure A).
- The device gives a single spray that should be delivered into 1 nostril.
- Never use more than 1 device or dose into more than 1 nostril.

- Keep TOSYMRA and all medicines out of reach of children.
- Do not remove the device from its packaging until ready to use.
- Do not test the spray or press the plunger before giving a dose into the nostril.
- Do not use after the expiration date has passed.

Storage Information

- The device should be stored at room temperature between 68° to 77°F (20° to 25°C).
- Do not store in the refrigerator or freezer.
- Always keep the device in the sealed blister package until time of use.

Instructions for Use

Step 1 – Gently Blow Your Nose

While sitting upright, gently blow your nose to clear your nostrils (See Figure B).

Step 2 – Remove 1 Device from Carton

Remove only 1 device from the carton (See Figure C).
Do not use more than 1 device to get your dose.

Step 3 – Check the Expiration Date on Back of Blister Package

Check the expiration date on the back of the blister package (See Figure D).
Do not use if the expiration date has passed. Throw away the expired device in the household trash if the expiration date has passed.

Step 4 – Remove Device from Blister Package

Peel off the paper backing completely from the blister package.
Flip the blister package onto your hand to remove the device from its packaging (See Figure E).

Step 5 – Check the Expiration Date on the Device

Check the expiration date on the device (See Figure F).
Do not use the device if the expiration date has passed. Throw away the expired device in the household trash if the expiration date has passed.

Step 6 – Close 1 Nostril

Gently press 1 nostril with your finger to keep it closed (See Figure G).

Step 7 – Place Spray Nozzle in Open Nostril

Hold the device upright between your thumb and first 2 fingers (See Figure H).
Insert half of the spray nozzle into the open nostril and angle outward (See Figure I).

Step 8 – Tilt Head Back Slightly

While keeping the device in your nose, tilt your head back slightly (See Figure J).
This will allow the medicine to go into your nasal passage without dripping out.

Step 9 – Deliver the Dose

As you slowly breathe through your nose, firmly press the plunger all the way up to release the dose (See Figure K).
Note: The plunger is stiff so make sure to press firmly.

Step 10 – Remove Device and Breathe Gently for 10 to 20 Seconds

Remove the device from your nostril. While keeping your head upright, gently breathe in through your nose and breathe out through your mouth. Repeat this for 10 to 20 seconds (See Figure L).
It is normal for you to feel liquid in your nose or at the back of your throat.
Do not look down because the medicine may drip from your nose.
Do not breathe in deeply.

Step 11 – Dispose of the Used Device

Throw away the used device and its packaging into your household trash (See Figure M).
You have received your full dose, if you have:

🗸 Used 1 device
🗸 Given 1 spray into 1 nostril

Manufactured for
TONIX MEDICINES, INC.
Chatham, NJ 07928
TOSYMRA is a registered trademark of Tonix Medicines, Inc.
This product may be covered by one or more U.S. patent(s).

This Instructions for Use has been approved by the U.S. Food and Drug Administration.

Revised: 10/2023

PRINCIPAL DISPLAY PANEL - 10 mg Bottle Blister Pack Carton

TONIX
MEDICINES

NDC 70792-812-61
Rx only

tosymra®
(sumatriptan nasal spray) 10 mg

This box contains six (6) unit-dose nasal spray devices.
Each unit-dose contains 10 mg of sumatriptan in 0.1 mL.

For Intranasal Use Only

1 spray per unit.
Do not test before use.